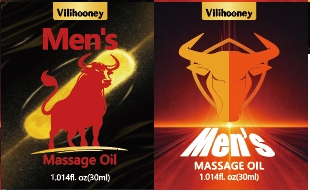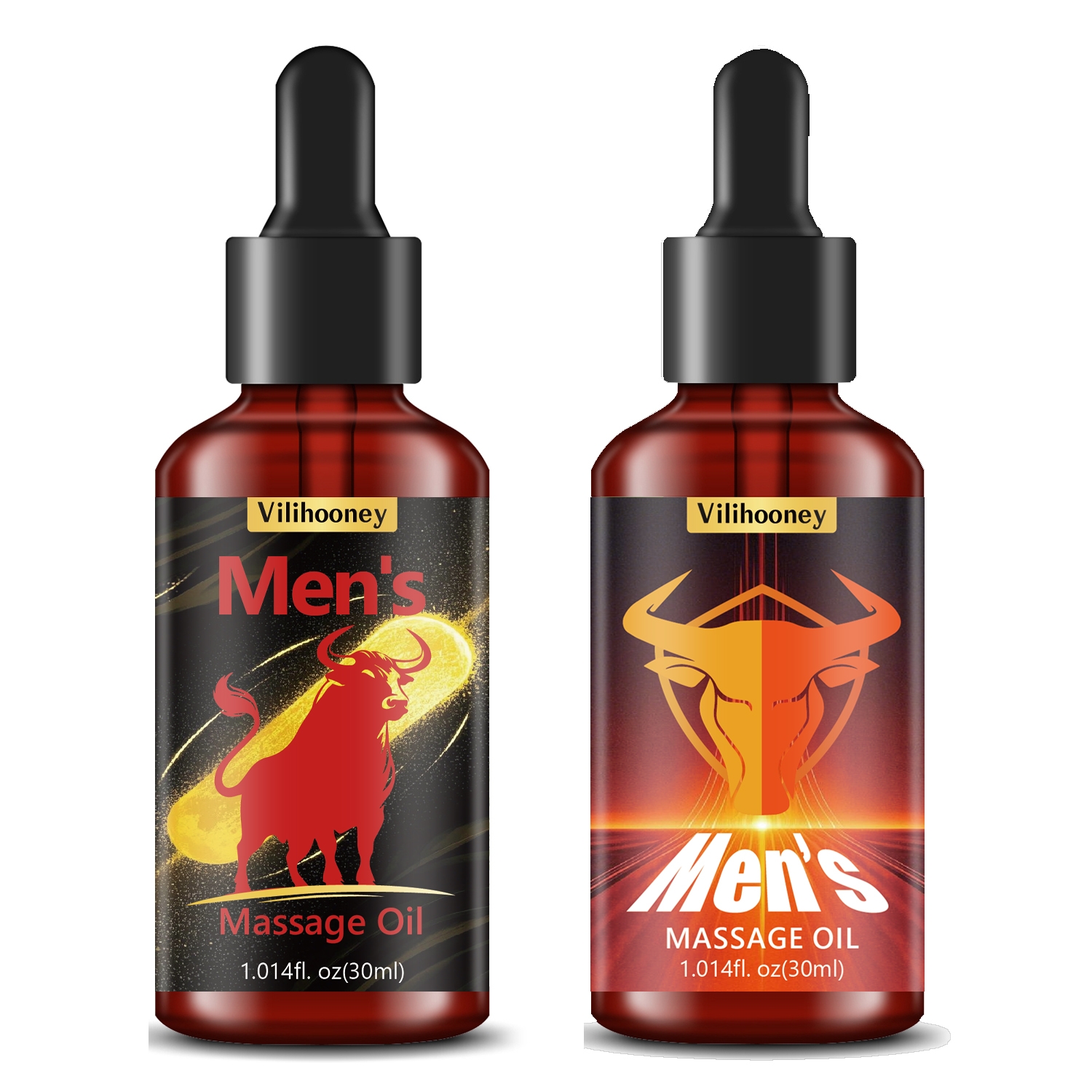 DRUG LABEL: Mens Massage Oil
NDC: 84025-303 | Form: LIQUID
Manufacturer: Guangzhou Yanxi Biotechnology Co., Ltd
Category: otc | Type: HUMAN OTC DRUG LABEL
Date: 20250106

ACTIVE INGREDIENTS: GLYCERIN 5 mg/30 mL; PANTHENOL 3 mg/30 mL
INACTIVE INGREDIENTS: WATER

DOSAGE AND ADMINISTRATION

Simply wash the penis, apply and gently massage until absorbed. lt will work for a short time.

WARNINGS

Keep out of children

INACTIVE INGREDIENT

Aqua

INDICATIONS AND USAGE

For daily skin care

Keep out of children

PURPOSE

Bigger and longer penis -Penile erectle cream can make the penis thicker, biger and longer. t can help you increase feelings of desire and enhance orgasm.